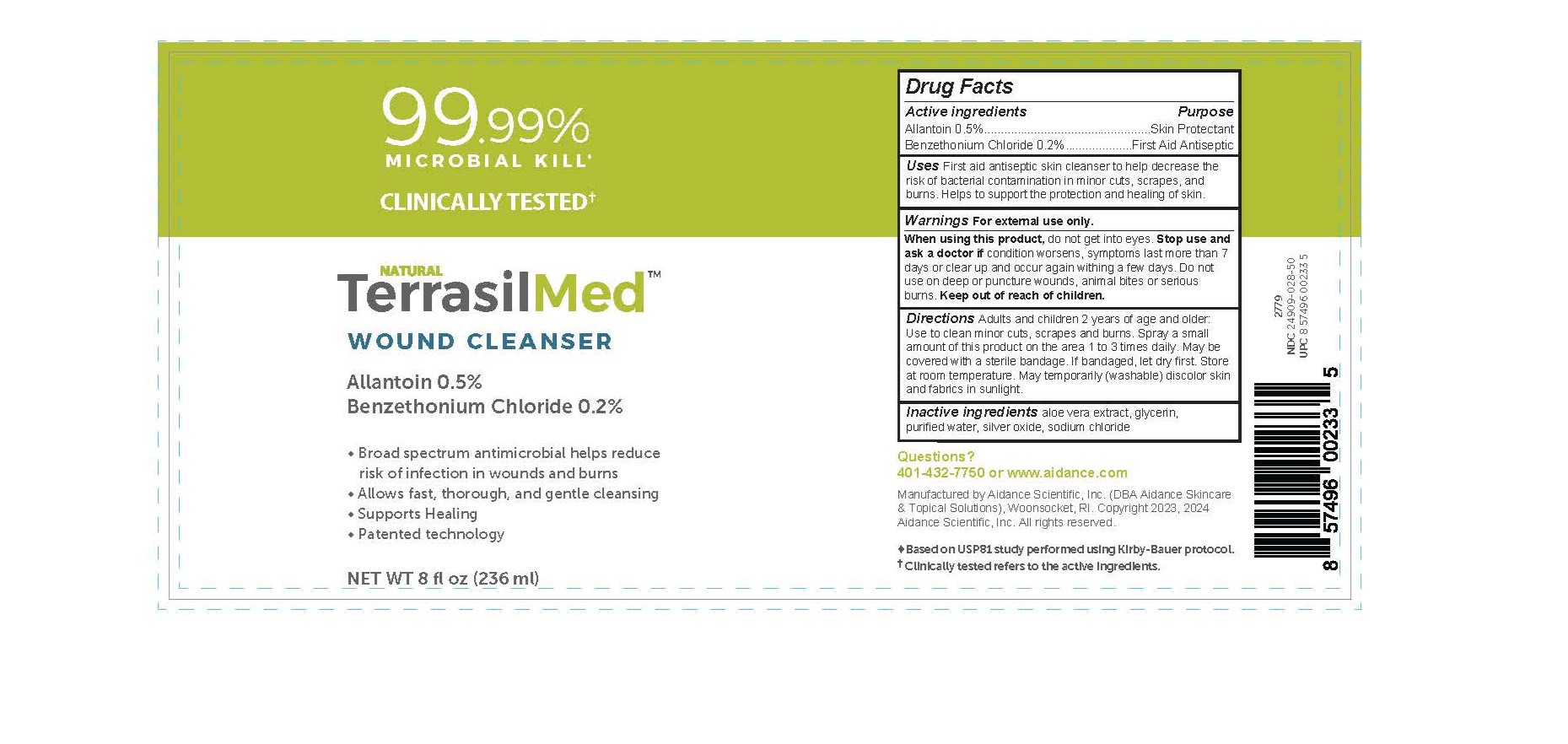 DRUG LABEL: TerrasilMed Wound Cleanser
NDC: 24909-028 | Form: OINTMENT
Manufacturer: Aidance Skincare & Topical Solutions, LLC
Category: otc | Type: HUMAN OTC DRUG LABEL
Date: 20240524

ACTIVE INGREDIENTS: ALLANTOIN 0.5 g/100 mL; BENZETHONIUM CHLORIDE 0.2 g/100 mL
INACTIVE INGREDIENTS: ALOE VERA LEAF; GLYCERIN; WATER; SILVER OXIDE; SODIUM CHLORIDE

24909-028 TerrasilMed Wound Cleanser

Active Ingredients Purpose

Allantoin 0.5% Skin Protectant
Benzethonium Chloride 0.2% First Aid Antiseptic

Uses

First aid antiseptic skin cleanser to help decrease the risk of bacterial contamination in minor cuts, scrapes, and burns. Helps to support the protection and healing of skin.

Warnings

For external use only

When using this product, do not get into eyes.

Stop use and ask a doctor if condition worsens, symptoms last more than 7 days or clear up and occur again within a few days.

Do not use on deep or puncture wounds, animal bites or serious burns.

Keep out of reach of children.

Directions

Adults and children 2 years of age and older: Use to clean minor cuts, scrapes, and burns. Spray a small amount of this product on the area 1 to 3 times daily. May be covered with a sterile bandage. If bandaged, let dry first. Store at room temperature. May temporarily (washable) discolor skin and fabrics in sunlight.

Inactive ingredients

aloe vera extract, glycerin, purified water, silver oxide, sodium chloride

Questions?

401-432-7750 or www.aidance.com